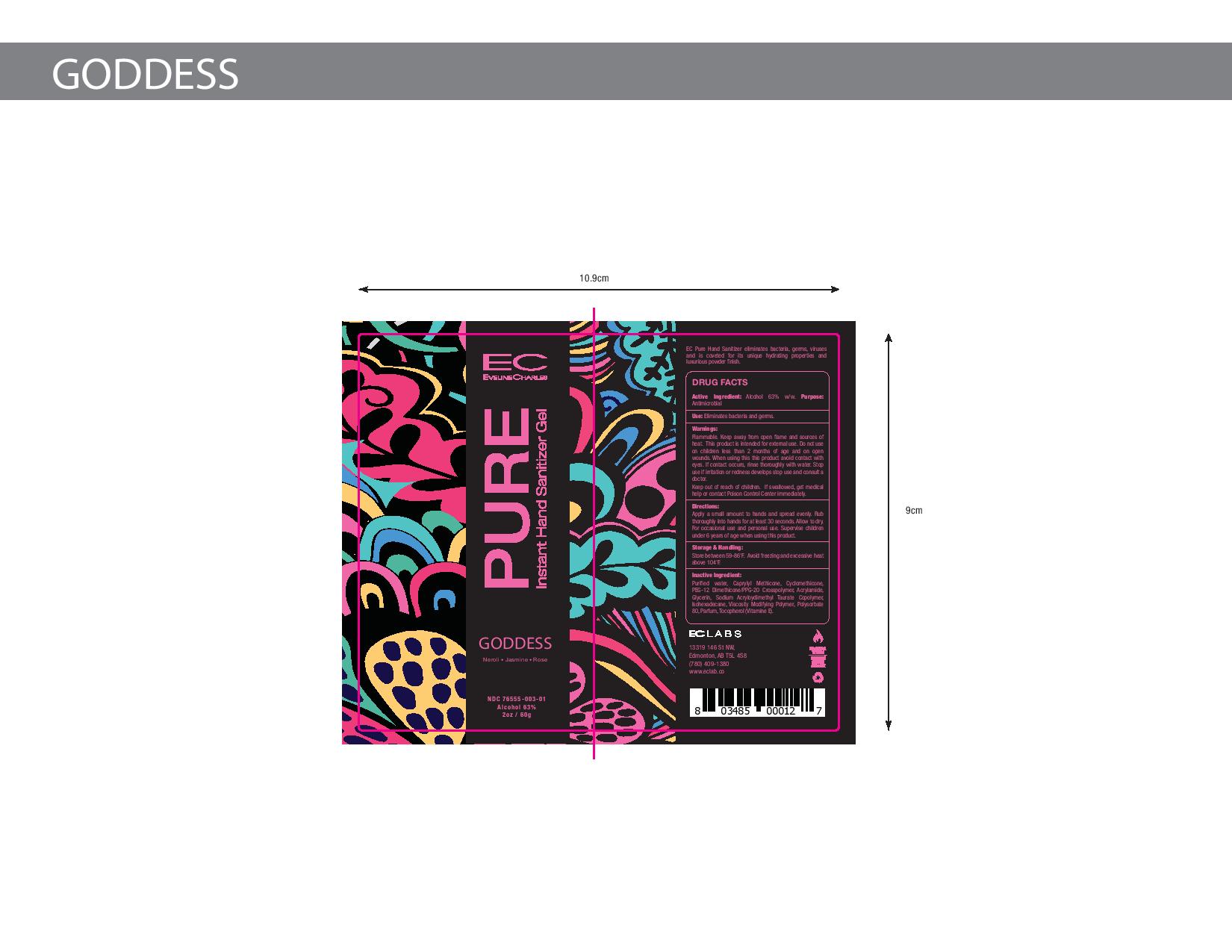 DRUG LABEL: EC Pure Instant Cream Hand Sanitizer Goddess
NDC: 76555-003 | Form: CREAM
Manufacturer: Ec Labs Inc.
Category: otc | Type: HUMAN OTC DRUG LABEL
Date: 20220114

ACTIVE INGREDIENTS: ALCOHOL 37.8 g/60 g
INACTIVE INGREDIENTS: SODIUM ACRYLOYLDIMETHYLTAURATE 1.74 g/60 g; CITRUS AURANTIUM FLOWER OIL 0.0072 g/60 g; CYCLOMETHICONE 1.02 g/60 g; AMMONIUM ACRYLOYLDIMETHYLTAURATE, DIMETHYLACRYLAMIDE, LAURYL METHACRYLATE AND LAURETH-4 METHACRYLATE COPOLYMER, TRIMETHYLOLPROPANE TRIACRYLATE CROSSLINKED (45000 MPA.S) 0.78 g/60 g; ROSA X DAMASCENA FLOWER OIL 0.0044 g/60 g; PEG/PPG-18/12 DIMETHICONE 5.1 g/60 g; MICHELIA CHAMPACA FLOWER 0.0042 g/60 g; ORANGE OIL 0.0167 g/60 g; GERANIUM OIL, ALGERIAN TYPE 0.0072 g/60 g; JASMINUM OFFICINALE FLOWER 0.0044 g/60 g; GLYCERIN 0.3 g/60 g; TOCOPHEROL 0.06 g/60 g; WATER 13.17 g/60 g

Eveline Charles Pure Instant Cream Hand Sanitizer Goddess

Active Ingredient(s)

Alcohol 63% w/w. Purpose: Antimicrobial

Purpose

Antimicrobial, Hand Sanitizer

Use

Eliminates bacteria and germs.

Warnings

Flammable. Keep away from open flame and sources of heat. This product is intended for external use only.

Do not use on children less than 2 months of age and on open skin wounds

When using this product avoid contact with eyes. If contact occurs, rinse thoroughly with water.

Stop use if irritation or redness develops stop use and consult a doctor.

Keep out of reach of children. If swallowed, get medical help or contact a Poison Control Center right away.

Directions

Apply a small amount to hands and spread evenly.

Rub thoroughly into hands for at least 30 seconds.

Allow to dry. For occasional and personal use.

Supervise children under 6 years of age when using this product.

Other information

- Store between 59-86F
- Avoid freezing and excessive heat above 104F

Inactive ingredients

glycerin, hydrogen peroxide, purified water USP

Package Label - Principal Display Panel

60g NDC:76555-003